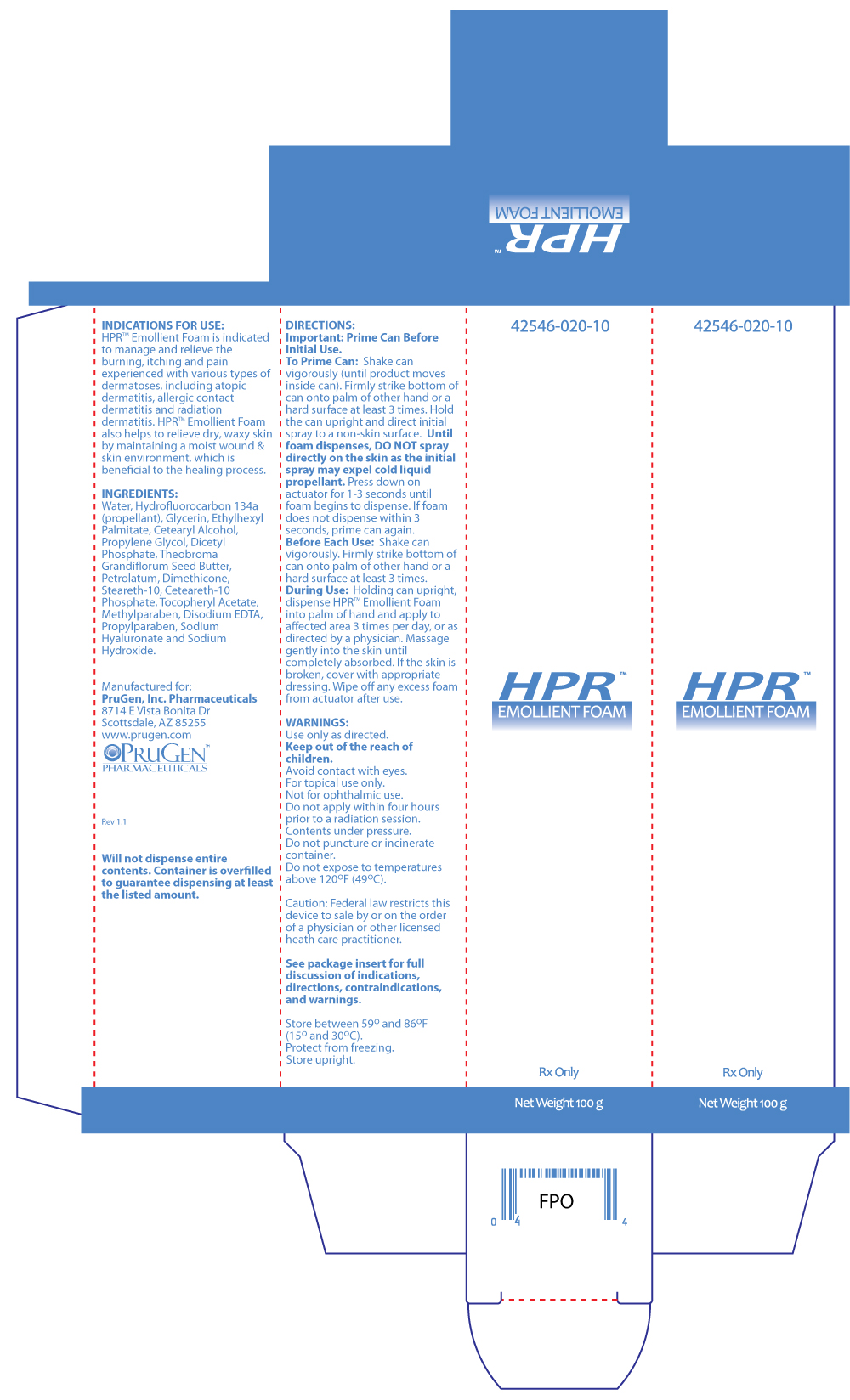 DRUG LABEL: HPR Emollient Foam
NDC: 42546-020
Manufacturer: PruGen, Inc.
Category: other | Type: PRESCRIPTION MEDICAL DEVICE LABEL
Date: 20120905

HPR Emollient Foam

INDICATIONS FOR USE

HPR Emollient Foam is indicated to manage and relieve the burning, itching and pain experienced with various types of dermatoses, including atopic dermatitis, allergic contact dermatitis and radiation dermatitis. HPR Emollient Foam also helps to relieve dry, waxy skin by maintaining a moist wound & skin environment, which is beneficial to the healing process.

CONTRAINDICATIONS

HPR Emollient Foam is contraindicated in persons with a known hypersensitivity to any of the components of the formulation.

WARNINGS

Use only as directed.

Keep out of the reach of children.

Avoid contact with eyes.

For topical use only.

Not for ophthalmic use.

Do not apply within four hours prior to a radiation session.

Contents under pressure.

Do not puncture or incinerate container.

Do not expose to temperatures above 120oF (49oC).

PRECAUTIONS AND OBSERVATIONS

• HPR Emollient Foam does not contain a sunscreen and should not be used prior to extended exposure to the sun.

• If clinical signs of infection are present, appropriate treatment should be initiated; use of HPR Emollient Foam may be continued during the anti-infective therapy.

• If the condition does not improve within 10-14 days, consult a physician.

• HPR Emollient Foam may dissolve fuchsin when this dye is used to define the margins of the radiation fields to be treated.

DIRECTIONS

Important: Prime Can Before Initial Use.

To Prime Can: Shake can vigorously (until product moves inside can). Firmly strike bottom of can onto palm of other hand or a hard surface at least 3 times. Hold the can upright and direct initial spray to a non-skin surface. Until foam dispenses, DO NOT spray directly on the skin as the initial spray may expel cold liquid propellant. Press down on actuator for 1-3 seconds until foam begins to dispense. If foam does not dispense within 3 seconds, prime can again.

Before Each Use: Shake can vigorously. Firmly strike bottom of can onto palm of other hand or a hard surface at least 3 times.

During Use: Holding can upright, dispense HPRTM Emollient Foam into palm of hand and apply to affected area 3 times per day, or as directed by a physician. Massage gently into the skin until completely absorbed. If the skin is broken, cover with appropriate dressing. Wipe off any excess foam from actuator after use.

INGREDIENTS

Water, Hydrofluorocarbon 134a (propellant), Glycerin, Ethylhexyl Palmitate, Cetearyl Alcohol, Propylene Glycol, Dicetyl Phosphate, Theobroma Grandiflorum Seed Butter, Petrolatum, Dimethicone, Steareth-10, Ceteareth-10 Phosphate, Tocopheryl Acetate, Methylparaben, Disodium EDTA, Propylparaben, Sodium Hyaluronate and Sodium Hydroxide.

HOW SUPPLIED

HPR Emollient Foam is available in a 100 g canister (NDC 42546-020-10).

Will not dispense entire contents. Container is overfilled to guarantee dispensing at least the listed amount.

Caution: Federal law restricts this device to sale by or on the order of a physician or other licensed heath care practitioner.

Store between 59o and 86oF (15o and 30oC). Protect from freezing. Store upright.

Manufactured for:

PruGen, Inc. Pharmaceuticals

8714 E Vista Bonita Dr

Scottsdale, AZ 85255

www.prugen.com

PR Cream Box Label

NDC 42546-135-04

PR cream Nonsteroidal Cream

For Topical Dermatological Use Only

Dispense as a complete kit

Kit includes:

-2 tubes PR cream - 2oz. (56.7g)

-2 tubes PruDrate moisturizing cream - 2oz. (56.7g)

- Patient Instructions

Rx Only

PruGen, Inc. Pharmaceuticals